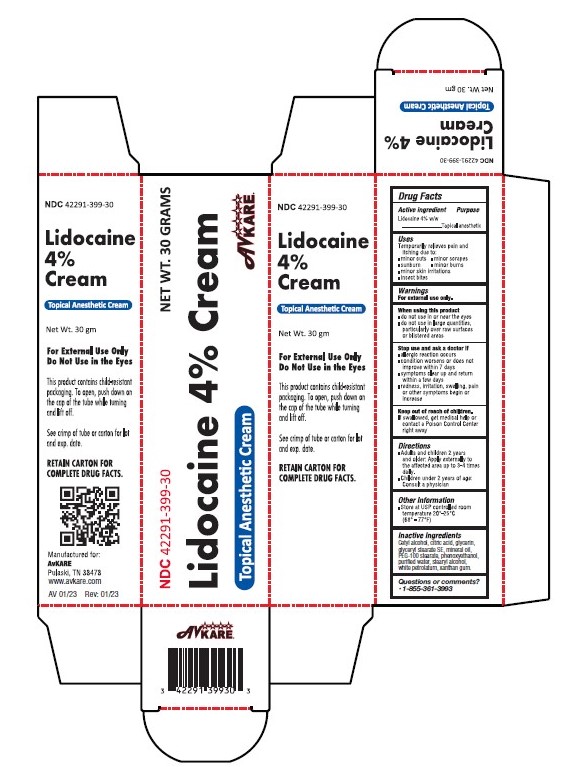 DRUG LABEL: Lidocaine
NDC: 42291-399 | Form: CREAM
Manufacturer: AvKARE
Category: otc | Type: HUMAN OTC DRUG LABEL
Date: 20260114

ACTIVE INGREDIENTS: LIDOCAINE 4 g/100 g
INACTIVE INGREDIENTS: PHENOXYETHANOL; MINERAL OIL; GLYCERYL STEARATE SE; CETYL ALCOHOL; GLYCERIN; PEG-100 STEARATE; XANTHAN GUM; WATER; STEARYL ALCOHOL; PETROLATUM; CITRIC ACID MONOHYDRATE

Lidocaine 4% Cream

Active Ingredient:

Lidocaine 4% w/w

Purpose

Topical anesthetic

Uses

temporarily relieves pain and itching due to:

- minor cuts
- minor scrapes
- sunburn
- minor skin irritations
- minor burns
- insect bites

WARNINGS

For external use only.

When using this product

- do not use in or near the eyes
- do not use in large quantities, particularly over raw surfaces or blistered areas

Stop use and ask doctor if

- Allergic reaction occurs
- condition worsens or does not improve within 7 days
- symptoms clear up and return within a few days
- redness, irritation, swelling, pain or other symptoms begin or increase

Keep out of reach of children.

If swallowed, get medical help or contact a Poison Control Center right away

Directions

- Adults and children 2 years and older: Apply externally to the affected area up to 3-4 times daily.
- Children under 2 years of age: Consult a doctor.

Other Information

Store at USP controlled room temperature 20-25 degC (68-77 deg.F).

Inactive ingredients

Cetyl alcohol, citric acid, glycerin, glyceryl stearate SE, mineral oil, PEG-100 stearate, phenoxyethanol, purified water, stearyl alcohol, white petrolatum, xanthan gum